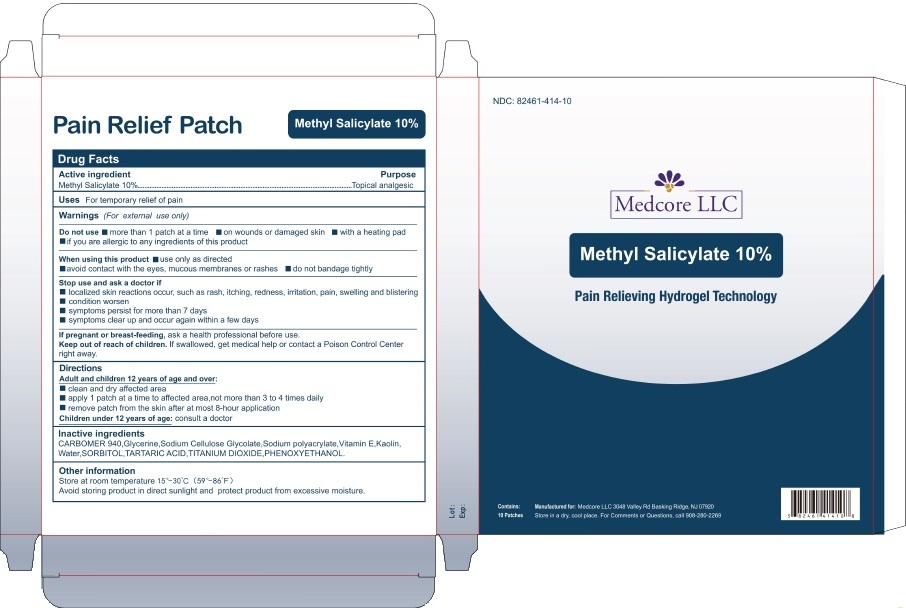 DRUG LABEL: Methyl Salicylate
NDC: 82461-414 | Form: PATCH
Manufacturer: Medcore LLC
Category: otc | Type: HUMAN OTC DRUG LABEL
Date: 20250714

ACTIVE INGREDIENTS: METHYL SALICYLATE 10 g/100 g
INACTIVE INGREDIENTS: CARBOMER 940; GLYCERIN; CARBOXYMETHYLCELLULOSE SODIUM, UNSPECIFIED; SODIUM POLYACRYLATE (8000 MW); .ALPHA.-TOCOPHEROL; KAOLIN; WATER; SORBITOL; TARTARIC ACID; TITANIUM DIOXIDE; PHENOXYETHANOL

Methyl Salicylate 10%
Pain Relief Patch

Active Ingredient Purpose

Methyl Salicylate 10% …………………………..…………………….….…Topical analgesic

INDICATIONS AND USAGE

Uses For temporary relief of pain

Warnings (For external use only)

Do not use

- more than 1 patch at a time
- on wounds or damaged skin
- with a heating pad
- if you are allergic to any ingredients of this product

When using this product

- use only as directed
- avoid contact with the eyes, mucous membranes or rashes
- do not bandage tightly

Stop use and ask a doctor if

- localized skin reactions occur, such as rash, itching, redness, irritation, pain, swelling and blistering
- condition worsen
- symptoms persist for more than 7 days
- symptoms clear up and occur again within a few days

If pregnant or breast-feeding, ask a health professional before use.

Keep out of reach of children. If swallowed, get medical help or contact a Poison Control Center right away.

Directions

Adult and children 12 years of age and over:

- clean and dry affected area
- apply 1 patch at a time to affected area, not more than 3 to 4 times daily
- remove patch from the skin after at most 8-hour application

Children under 12 years of age: consult a doctor

Inactive ingredients

CARBOMER 940, Glycerine, Sodium Cellulose Glycolate, Sodium polyacrylate, Vitamin E, Kaolin, Water, SORBITOL, TARTARIC ACID, TITANIUM DIOXIDE, PHENOXYETHONOL.

Other information

Store at room temperature 15°-30°C (59°-86°F)
Avoid storing product in direct sunlight and protect product from excessive moisture.

PRINCIPAL DISPLAY PANEL

NDC: 82461-414-10

Medcore LLC

Methyl Salicylate 10%

Pain Relieving Hydrogel Technology

Contains:
10 Patches

Manufactured for: Medcore LLC 3048 Valley Rd Basking Ridge, NJ 07920
Store in a dry, cool place. For Comments or Questions, call 908-280-2269